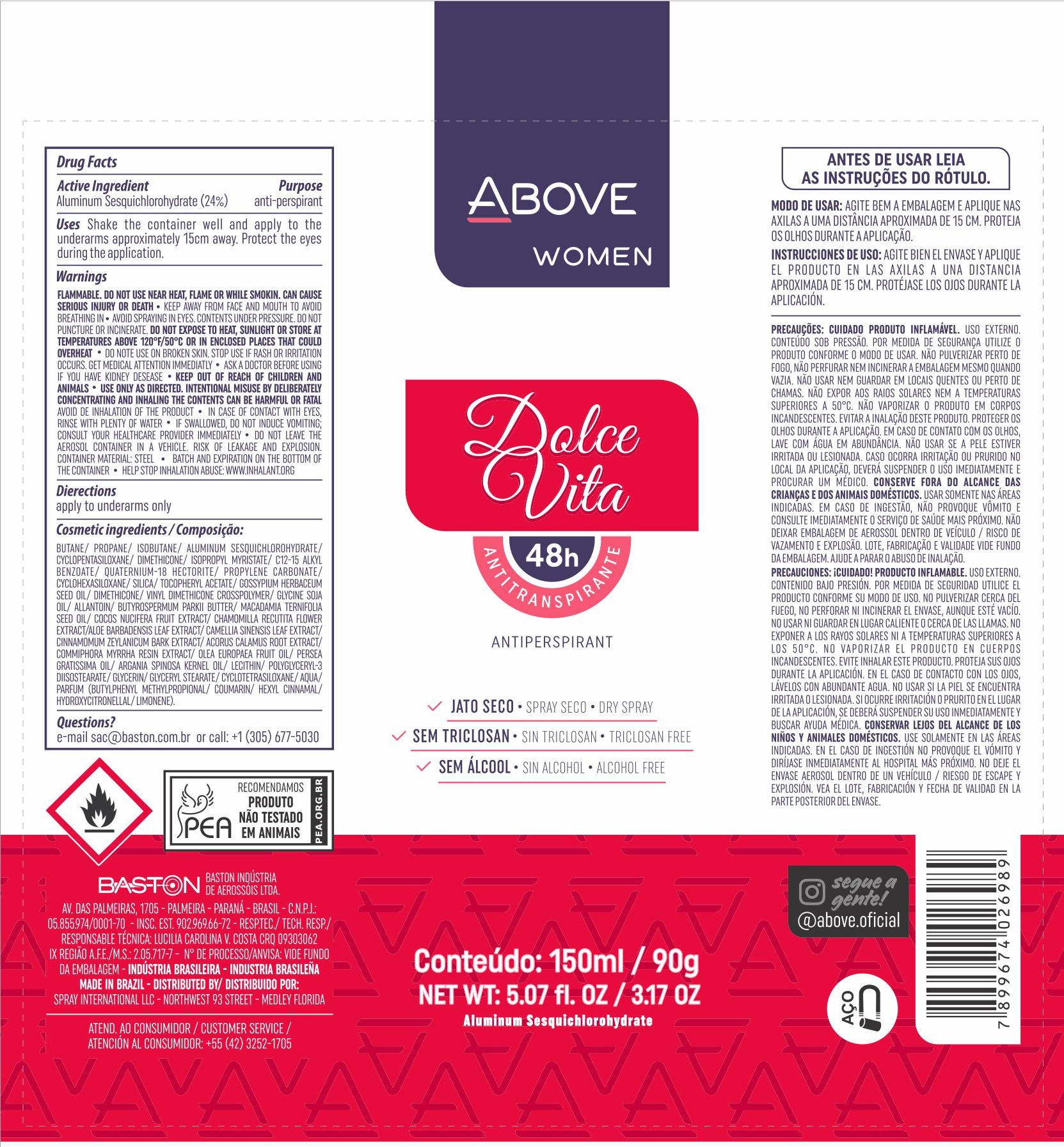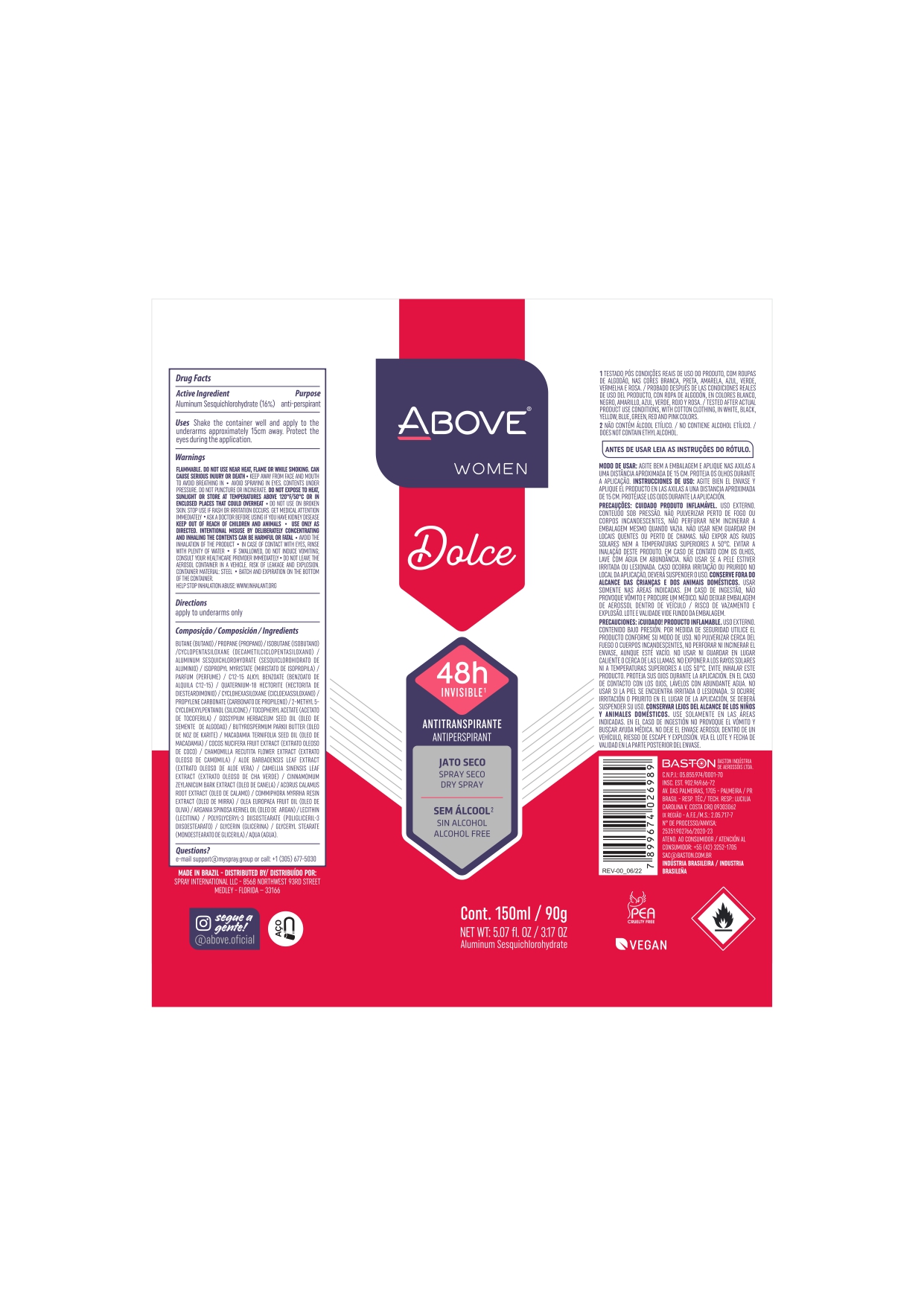 DRUG LABEL: Antiperspirant Above Dolce Vita
NDC: 73306-1107 | Form: AEROSOL, SPRAY
Manufacturer: Baston Industria de Aerossóis Ltda
Category: otc | Type: HUMAN OTC DRUG LABEL
Date: 20240503

ACTIVE INGREDIENTS: ALUMINUM SESQUICHLOROHYDRATE 24 g/100 g
INACTIVE INGREDIENTS: POLYGLYCERYL-3 DIISOSTEARATE; COCONUT; ACORUS CALAMUS ROOT; PROPANE; ARGAN OIL; GLYCERYL MONOSTEARATE; SHEA BUTTER; PROPYLENE CARBONATE; ISOBUTANE; ALOE VERA LEAF; LEVANT COTTON SEED; BUTANE; CHAMOMILE; VINYL DIMETHICONE/METHICONE SILSESQUIOXANE CROSSPOLYMER; ISOPROPYL MYRISTATE; CYCLOMETHICONE 5; MYRRH OIL; DIMETHICONE; SILICA DIMETHYL SILYLATE; ALLANTOIN; MACADAMIA OIL; LECITHIN, SOYBEAN; DISTEARDIMONIUM HECTORITE; WATER; GREEN TEA LEAF; AVOCADO OIL; CINNAMON BARK OIL; GLYCERIN; .ALPHA.-TOCOPHEROL ACETATE

Antiperspirant Above Dolce Vita Aerosol